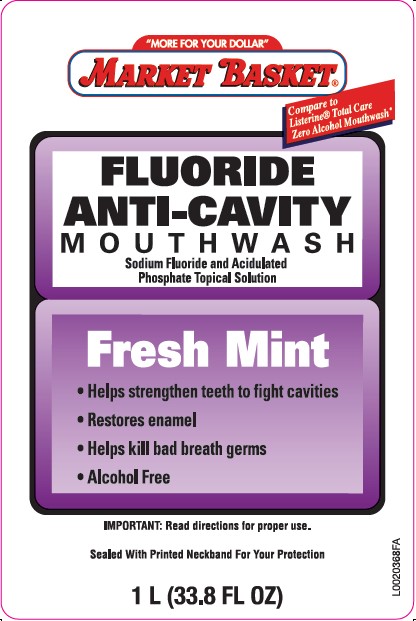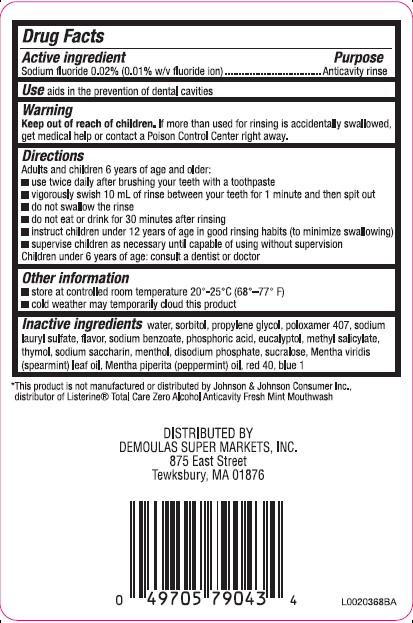 DRUG LABEL: Anticavity
NDC: 53942-971 | Form: RINSE
Manufacturer: Demoulas Super Markets, Inc
Category: otc | Type: HUMAN OTC DRUG LABEL
Date: 20260203

ACTIVE INGREDIENTS: SODIUM FLUORIDE 0.1 mg/1 mL
INACTIVE INGREDIENTS: WATER; SORBITOL; PROPYLENE GLYCOL; POLOXAMER 407; SODIUM LAURYL SULFATE; SODIUM BENZOATE; PHOSPHORIC ACID; EUCALYPTOL; METHYL SALICYLATE; THYMOL; SACCHARIN SODIUM; MENTHOL; SODIUM PHOSPHATE, DIBASIC, ANHYDROUS; SUCRALOSE; SPEARMINT OIL; PEPPERMINT OIL; FD&C RED NO. 40; FD&C BLUE NO. 1

Market Basket 971.001/971AB
Tartar Control Plus Antiseptic Mouth Rinse, Blue Mint

Active Ingredients

Sodium fluoride 0.02% (0.01% w/v fluoride ion)

Purpose

Anticavity rinse

Use

aids in the prevention of dental cavities

Warning

for this product

Keep out of Reach of Children.

If more than used for rinsing is accidentally swallowed, get medical help or contact a Poison Control Center right away.

Directions

Adults and children 6 years of age and older:

- use twice daily after brushing your teeth with a toothpaste
- vigorously swish 10 mL (2 teaspoonfuls) of rinse between your teeth for 1 minute and then spit out.
- do not swallow the rinse
- do not eat or drink for 30 minutes after rinsing
- instruct children under 12 years of age in good rinsing habits (to minimize swallowing)
- supervise children as necessary until capable of using without supervision

Children under 6 years of age: consult a dentist or doctor

Other information

- store at controlled room temperature 20° - 25°C (68° - 77° F)
- cold weather may temporarily cloud this product

Inactive ingredients

water, sorbitol, propylene glycol, poloxamer 407, sodium lauryl sulfate, flavor, sodium benzoate, phosphoric acid, eucalyptol, methyl salicylate, thymol, sodium saccharin, menthol, disodium phosphate, sucralose, Mentha viridis (spearmint) leaf oil, Mentha piperita (peppermint) oil, red 40, blue 1

Disclaimer

*This product is not manufactured or distributed by Johnson & Johnson Consumer Inc. distributor of ListerineTotal Care Zero Alcohol Anticavity Fresh Mint Mouthwash.

Adverse reactions section

DISTRIBUTED BY

DEMOULAS SUPER MARKETS, INC.

875 East Street

Tewksbury, MA 01876

PRINCIPAL DISPLAY PANEL

"MORE FOR YOUR DOLLAR"

MARKET BASKET®

Compare to Listerine®Total Care Zero Alcohol Mouthwash*

FLOURIDE

ANTI-CAVITY

MOUTHWASH

Sodium fluoride and Acidulated Phosphate Topical Solution

Fresh Mint

- Helps strengthen teeth to fight cavities
- Restores enamel
- Helps kill bad breath germs
- Alcohol Free

IMPORTANT: Read directions for proper use.

Sealed With Printed Neckband For our Protection

1 L (33.8 FL OZ)